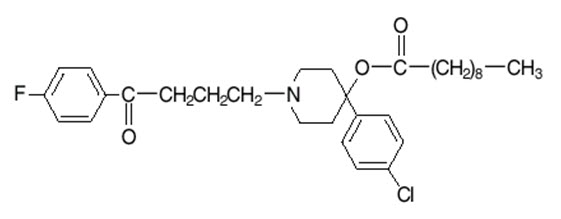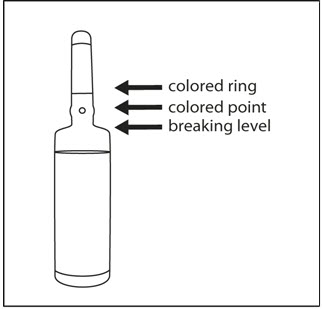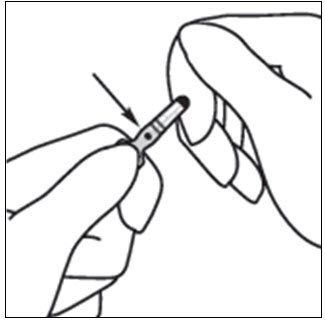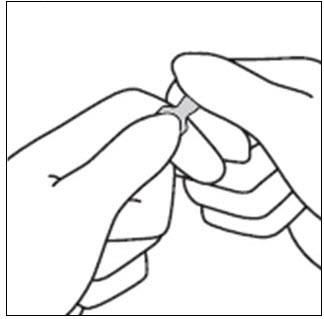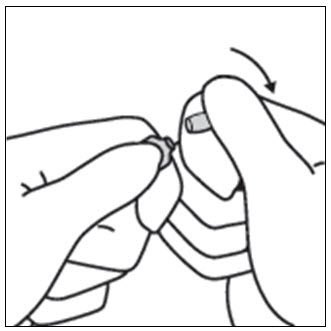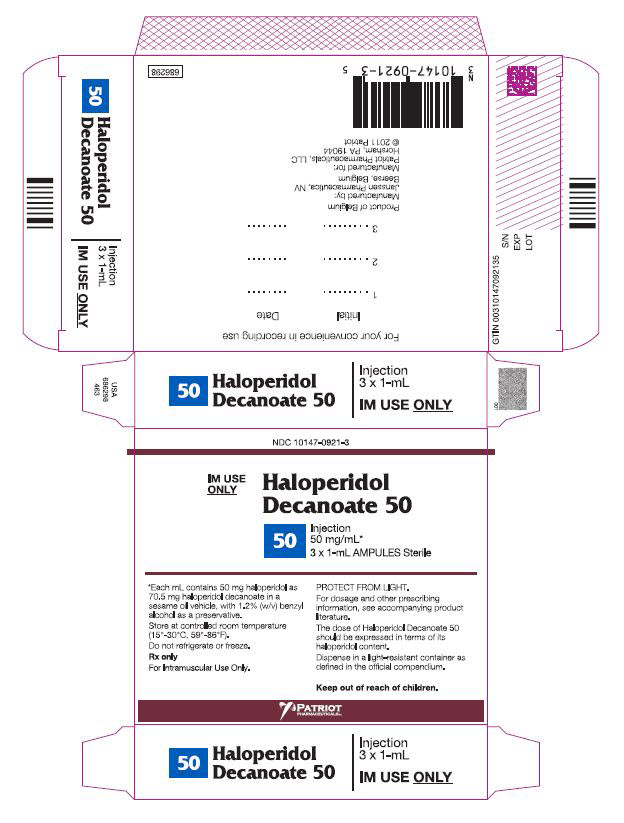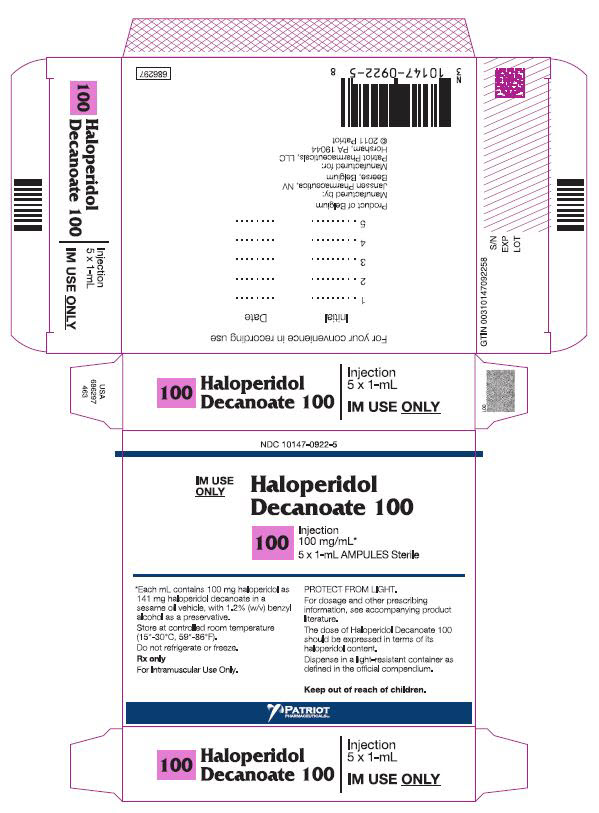 DRUG LABEL: Haloperidol Decanoate
NDC: 10147-0921 | Form: INJECTION
Manufacturer: Patriot Pharmaceuticals LLC
Category: prescription | Type: HUMAN PRESCRIPTION DRUG LABEL
Date: 20250219

ACTIVE INGREDIENTS: HALOPERIDOL DECANOATE 50 mg/1 mL
INACTIVE INGREDIENTS: SESAME OIL; BENZYL ALCOHOL

HALOPERIDOL DECANOATE 50
HALOPERIDOL DECANOATE 100
For IM Injection Only

WARNING

Increased Mortality in Elderly Patients with Dementia-Related Psychosis

Elderly patients with dementia-related psychosis treated with antipsychotic drugs are at an increased risk of death. Analyses of seventeen placebo-controlled trials (modal duration of 10 weeks), largely in patients taking atypical antipsychotic drugs, revealed a risk of death in drug-treated patients of between 1.6 to 1.7 times the risk of death in placebo-treated patients. Over the course of a typical 10-week controlled trial, the rate of death in drug-treated patients was about 4.5%, compared to a rate of about 2.6% in the placebo group. Although the causes of death were varied, most of the deaths appeared to be either cardiovascular (e.g., heart failure, sudden death) or infectious (e.g., pneumonia) in nature. Observational studies suggest that, similar to atypical antipsychotic drugs, treatment with conventional antipsychotic drugs may increase mortality. The extent to which the findings of increased mortality in observational studies may be attributed to the antipsychotic drug as opposed to some characteristic(s) of the patients is not clear. Haloperidol decanoate is not approved for the treatment of patients with dementia-related psychosis (see WARNINGS).

DESCRIPTION

Haloperidol decanoate is the decanoate ester of the butyrophenone, haloperidol. It has a markedly extended duration of effect. It is available in sesame oil in sterile form for intramuscular (IM) injection. The structural formula of haloperidol decanoate, 4-(4-chlorophenyl)-1-[4-(4-fluorophenyl)-4-oxobutyl]-4 piperidinyl decanoate, is:

Haloperidol decanoate is almost insoluble in water (0.01 mg/mL), but is soluble in most organic solvents.

Each mL of Haloperidol decanoate 50 for IM injection contains 50 mg haloperidol (present as haloperidol decanoate 70.52 mg) in a sesame oil vehicle, with 1.2% (w/v) benzyl alcohol as a preservative.

Each mL of Haloperidol decanoate 100 for IM injection contains 100 mg haloperidol (present as haloperidol decanoate 141.04 mg) in a sesame oil vehicle, with 1.2% (w/v) benzyl alcohol as a preservative.

CLINICAL PHARMACOLOGY

Haloperidol decanoate 50 and Haloperidol decanoate 100 are the long-acting forms of haloperidol, an antipsychotic. The mechanism of action of haloperidol for the treatment of schizophrenia is unclear. However, its efficacy could be mediated through its activity as an antagonist at central dopamine type 2 receptors. Haloperidol also binds to alpha-1 adrenergic receptors, but with lower affinity, and displays minimal binding to muscarinic cholinergic and histaminergic (H1) receptors. Administration of haloperidol decanoate in sesame oil results in slow and sustained release of haloperidol. The plasma concentrations of haloperidol gradually rise, reaching a peak at about 6 days after the injection, and falling thereafter, with an apparent half-life of about 3 weeks. Steady state plasma concentrations are achieved within 2 to 4 months in patient receiving monthly injections. The relationship between dose of haloperidol decanoate and plasma haloperidol concentration is roughly linear for doses below 450 mg. It should be noted, however, that the pharmacokinetics of haloperidol decanoate following intramuscular injections can be quite variable between subjects.

INDICATIONS AND USAGE

Haloperidol decanoate 50 and Haloperidol decanoate 100 are indicated for the treatment of patients with schizophrenia who require prolonged parenteral antipsychotic therapy.

CONTRAINDICATIONS

Since the pharmacologic and clinical actions of Haloperidol decanoate 50 and Haloperidol decanoate 100 are attributed to haloperidol as the active medication, Contraindications, Warnings, and additional information are those of haloperidol, modified only to reflect the prolonged action.

Haloperidol is contraindicated in patients with:

- Severe toxic central nervous system depression or comatose states from any cause.
- Hypersensitivity to this drug – hypersensitivity reactions have included anaphylactic reaction and angioedema (see WARNINGS, Hypersensitivity Reactionsand ADVERSE REACTIONS).
- Parkinson's disease (see WARNINGS, Neurological Adverse Reactions in Patients with Parkinson's Disease or Dementia with Lewy Bodies).
- Dementia with Lewy bodies (see WARNINGS, Neurological Adverse Reactions in Patients with Parkinson's Disease or Dementia with Lewy Bodies).

WARNINGS

Increased Mortality in Elderly Patients with Dementia-Related Psychosis

Elderly patients with dementia-related psychosis treated with antipsychotic drugs are at an increased risk of death. Haloperidol decanoate is not approved for the treatment of patients with dementia-related psychosis (see BOXED WARNING).

Cardiovascular Effects

Cases of sudden death, QTc interval-prolongation, and Torsades de Pointes have been reported in patients receiving haloperidol (see ADVERSE REACTIONS). Higher than recommended doses of any formulation and intravenous administration of haloperidol appear to be associated with a higher risk of QTc interval-prolongation and Torsades de Pointes. Also, a QTc interval that exceeds 500 msec is associated with an increased risk of Torsades de Pointes. Although cases have been reported even in the absence of predisposing factors, particular caution is advised in treating patients with other QTc-prolonging conditions (including electrolyte imbalance [particularly hypokalemia and hypomagnesemia], drugs known to prolong QTc, underlying cardiac abnormalities, hypothyroidism, and familial long QT-syndrome). HALOPERIDOL DECANOATEMUST NOT BE ADMINISTERED INTRAVENOUSLY.

Tachycardia and hypotension (including orthostatic hypotension) have also been reported in occasional patients (see ADVERSE REACTIONS).

Cerebrovascular Adverse Reactions

In controlled trials, elderly patients with dementia-related psychosis treated with some antipsychotics had an increased risk (compared to placebo) of cerebrovascular adverse reactions (e.g., stroke, transient ischemic attack), including fatalities. The mechanism for this increased risk is not known. An increased risk cannot be excluded for haloperidol decanoate, other antipsychotics, or other patient populations. Haloperidol decanoate should be used with caution in patients with risk factors for cerebrovascular adverse reactions.

Tardive Dyskinesia

A syndrome consisting of potentially irreversible, involuntary, dyskinetic movements may develop in patients treated with antipsychotic drugs (see ADVERSE REACTIONS). Although the prevalence of the syndrome appears to be highest among the elderly, especially elderly women, it is impossible to rely upon prevalence estimates to predict, at the inception of antipsychotic treatment, which patients are likely to develop the syndrome. Whether antipsychotic drug products differ in their potential to cause tardive dyskinesia is unknown.

Both the risk of developing tardive dyskinesia and the likelihood that it will become irreversible are believed to increase as the duration of treatment and the total cumulative dose of antipsychotic drugs administered to the patient increase. However, the syndrome can develop, although much less commonly, after relatively brief treatment periods at low doses.

Tardive dyskinesia, may remit, partially or completely, if antipsychotic treatment is discontinued. Antipsychotic treatment, itself, however, may suppress (or partially suppress) the signs and symptoms of the syndrome and thereby may possibly mask the underlying process. The effect that symptomatic suppression has upon the long-term course of the syndrome is unknown.

Given these considerations, antipsychotic drugs should be prescribed in a manner that is most likely to minimize the occurrence of tardive dyskinesia. Chronic antipsychotic treatment should generally be reserved for patients who suffer from a chronic illness that 1) is known to respond to antipsychotic drugs, and 2) for whom alternative, equally effective, but potentially less harmful treatments are notavailable or appropriate. In patients who do require chronic treatment, the smallest dose and the shortest duration of treatment producing a satisfactory clinical response should be sought. The need for continued treatment should be reassessed periodically.

If signs and symptoms of tardive dyskinesia appear in a patient on antipsychotics, drug discontinuation should be considered. However, some patients may require treatment despite the presence of the syndrome.

Neuroleptic Malignant Syndrome (NMS)

A potentially fatal symptom complex sometimes referred to as Neuroleptic Malignant Syndrome (NMS) has been reported in association with antipsychotic drugs (see ADVERSE REACTIONS). Clinical manifestations of NMS are hyperpyrexia, muscle rigidity, altered mental status (including catatonic signs) and evidence of autonomic instability (irregular pulse or blood pressure, tachycardia, diaphoresis, and cardiac dysrhythmias). Additional signs may include elevated creatine phosphokinase, myoglobinuria (rhabdomyolysis) and acute renal failure.

The diagnostic evaluation of patients with this syndrome is complicated. In arriving at a diagnosis, it is important to identify cases where the clinical presentation includes both serious medical illness (e.g., pneumonia, systemic infection, etc.) and untreated or inadequately treated extrapyramidal signs and symptoms. Other important considerations in the differential diagnosis include central anticholinergic toxicity, heat stroke, drug fever and primary central nervous system (CNS) pathology.

The management of NMS should include 1) immediate discontinuation of antipsychotic drugs and other drugs not essential to concurrent therapy, 2) intensive symptomatic treatment and medical monitoring, and 3) treatment of any concomitant serious medical problems for which specific treatments are available. There is no general agreement about specific pharmacological treatment regimens for uncomplicated NMS.

If a patient requires antipsychotic drug treatment after recovery from NMS, the potential reintroduction of drug therapy should be carefully considered. The patient should be carefully monitored, since recurrences of NMS have been reported.

Hyperpyrexia and heat stroke, not associated with the above symptom complex, have also been reported with haloperidol.

Neurological Adverse Reactions in Patients with Parkinson's Disease or Dementia with Lewy Bodies

Patients with Parkinson's Disease or Dementia with Lewy Bodies are reported to have an increased sensitivity to antipsychotic medication. Manifestations of this increased sensitivity with haloperidol treatment include severe extrapyramidal symptoms, confusion, sedation, and falls. In addition, haloperidol may impair the antiparkinson effects of levodopa and other dopamine agonists. Haloperidol decanoate 50 and Haloperidol decanoate 100 are contraindicated in patients with Parkinson's Disease or Dementia with Lewy Bodies (see CONTRAINDICATIONS).

Hypersensitivity Reactions

There have been postmarketing reports of hypersensitivity reactions with haloperidol. These include anaphylactic reaction, angioedema, dermatitis exfoliative, hypersensitivity vasculitis, rash, urticaria, face edema, laryngeal edema, bronchospasm, and laryngospasm (see ADVERSE REACTIONS). Haloperidol decanoate 50 and Haloperidol decanoate 100 are contraindicated in patients with hypersensitivity to this drug (see CONTRAINDICATIONS).

Falls

Motor instability, somnolence, and orthostatic hypotension have been reported with the use of antipsychotics, including Haloperidol decanoate, which may lead to falls and, consequently, fractures or other fall-related injuries. For patients, particularly the elderly, with diseases, conditions, or medications that could exacerbate these effects, assess the risk of falls when initiating antipsychotic treatment and recurrently during treatment.

Combined Use of Haloperidol and Lithium

An encephalopathic syndrome (characterized by weakness, lethargy, fever, tremulousness and confusion, extrapyramidal symptoms, leukocytosis, elevated serum enzymes, BUN, and fasting blood sugar) followed by irreversible brain damage has occurred in a few patients treated with lithium plus haloperidol. A causal relationship between these events and the concomitant administration of lithium and haloperidol has not been established; however, patients receiving such combined therapy should be monitored closely for early evidence of neurological toxicity and treatment discontinued promptly if such signs appear.

General

A number of cases of bronchopneumonia, some fatal, have followed the use of antipsychotic drugs, including haloperidol. It has been postulated that lethargy and decreased sensation of thirst due to central inhibition may lead to dehydration, hemoconcentration and reduced pulmonary ventilation. Therefore, if the above signs and symptoms appear, especially in the elderly, the physician should institute remedial therapy promptly.

Although not reported with haloperidol, decreased serum cholesterol and/or cutaneous and ocular changes have been reported in patients receiving chemically-related drugs.

PRECAUTIONS

Leukopenia, Neutropenia, and Agranulocytosis

Class Effect

In clinical trial and/or postmarketing experience, events of leukopenia/neutropenia have been reported temporally related to antipsychotic agents, including Haloperidol decanoate. Agranulocytosis has also been reported.

Possible risk factors for leukopenia/neutropenia include pre-existing low white blood cell count (WBC) and history of drug-induced leukopenia/neutropenia. Patients with a history of a clinically significant low WBC or a drug-induced leukopenia/neutropenia should have their complete blood count (CBC) monitored frequently during the first few months of therapy and discontinuation of Haloperidol decanoate should be considered at the first sign of a clinically significant decline in WBC in the absence of other causative factors.

Patients with clinically significant neutropenia should be carefully monitored for fever or other symptoms or signs of infection and treated promptly if such symptoms or signs occur. Patients with severe neutropenia (absolute neutrophil count <1000/mm^3) should discontinue Haloperidol decanoate and have their WBC followed until recovery.

Other

Haloperidol decanoate 50 and Haloperidol decanoate 100 should be administered cautiously to patients:

- with severe cardiovascular disorders, because of the possibility of transient hypotension and/or precipitation of anginal pain. Should hypotension occur and a vasopressor be required, epinephrine must not be used since haloperidol may block its vasopressor activity, and paradoxical further lowering of the blood pressure may occur. Instead, metaraminol, phenylephrine or norepinephrine should be used.
- receiving anticonvulsant medications, with a history of seizures, or with EEG abnormalities, because haloperidol may lower the convulsive threshold. If indicated, adequate anticonvulsant therapy should be concomitantly maintained.
- with known allergies, or with a history of allergic reactions to drugs.
- receiving anticoagulants, since an isolated instance of interference occurred with the effects of one anticoagulant (phenindione).

Haloperidol may impair the antiparkinson effects of levodopa and other dopamine agonists. If concomitant antiparkinson medication is required, it may have to be continued after Haloperidol decanoate 50 or Haloperidol decanoate 100 is discontinued because of the prolonged action of haloperidol decanoate. If both drugs are discontinued simultaneously, extrapyramidal symptoms may occur. The physician should keep in mind the possible increase in intraocular pressure when anticholinergic drugs, including antiparkinson agents, are administered concomitantly with Haloperidol decanoate.

When Haloperidol decanoate is used to control mania in cyclic disorders, there may be a rapid mood swing to depression.

Severe neurotoxicity (rigidity, inability to walk or talk) may occur in patients with thyrotoxicosis who are also receiving antipsychotic medication, including Haloperidol.

Information for Patients

Haloperidol decanoate may impair the mental and/or physical abilities required for the performance of hazardous tasks such as operating machinery or driving a motor vehicle. The ambulatory patient should be warned accordingly.

The use of alcohol with this drug should be avoided due to possible additive effects and hypotension.

Drug Interactions

Drug-drug interactions can be pharmacodynamic (combined pharmacologic effects) or pharmacokinetic (alteration of plasma levels). The risks of using haloperidol in combination with other drugs have been evaluated as described below.

Pharmacodynamic Interactions

Since QTc interval-prolongation has been observed during haloperidol treatment, caution is advised when prescribing to a patient with QT-prolongation conditions or to patients receiving medications known to prolong the QTc-interval (see WARNINGS, Cardiovascular Effects). Examples include (but are not limited to): Class 1A antiarrhythmics (e.g., procainamide, quinidine, disopyramide); Class 3 antiarrhythmics (e.g., amiodarone, sotalol); and other drugs such as citalopram, erythromycin, levofloxacin, methadone, and ziprasidone.

Caution is advised when haloperidol decanoate is used in combination with drugs known to cause electrolyte imbalance (e.g., diuretics or corticosteroids) because hypokalemia, hypomagnesemia, and hypocalcemia are risk factors for QT prolongation.

As with other antipsychotic agents, it should be noted that haloperidol may be capable of potentiating CNS depressants such as anesthetics, opioids, and alcohol.

Pharmacokinetic Interactions

Drugs that May Increase Haloperidol Plasma Concentrations

Haloperidol is metabolized by several routes. The major pathways are glucuronidation and ketone reduction. The cytochrome P450 enzyme system is also involved, particularly CYP3A4 and, to a lesser extent, CYP2D6. Inhibition of these routes of metabolism by another drug or a decrease in CYP2D6 enzyme may result in increased haloperidol concentrations. The effect of CYP3A4 inhibition and of decreased CYP2D6 enzyme may be additive.

The haloperidol plasma concentrations increased when a CYP3A4 and/or CYP2D6 inhibitor was coadministered with haloperidol. Examples include:

- CYP3A4 inhibitors – alprazolam; itraconazole, ketoconazole, nefazodone, ritonavir.
- CYP2D6 inhibitors – chlorpromazine; promethazine; quinidine; paroxetine, sertraline, venlafaxine.
- Combined CYP3A4 and CYP2D6 inhibitors – fluoxetine, fluvoxamine; ritonavir.
- Buspirone.

Increased haloperidol plasma concentrations may result in an increased risk of adverse events, including QTc interval prolongation (see WARNINGS – Cardiovascular Effects). Increases in QTc have been observed when haloperidol was given with a combination of the metabolic inhibitors ketoconazole (400 mg/day) and paroxetine (20 mg/day).

It is recommended that patients who take haloperidol concomitantly with such medicinal products be monitored for signs or symptoms of increased or prolonged pharmacologic effects of haloperidol, and the haloperidol decanoate dose be decreased as deemed necessary.Valproate: Sodium valproate, a drug known to inhibit glucuronidation, does not affect haloperidol plasma concentrations.

Drugs that May Decrease Haloperidol Plasma Concentrations

Coadministration of haloperidol with potent enzyme inducers of CYP3A4 may gradually decrease the plasma concentrations of haloperidol to such an extent that efficacy may be reduced. Examples include (but are not limited to): carbamazepine, phenobarbital, phenytoin, rifampin, St John's Wort (Hypericum, perforatum).

Rifampin

In a study of 12 patients with schizophrenia coadministered oral haloperidol and rifampin, plasma haloperidol levels were decreased by a mean of 70% and mean scores on the Brief Psychiatric Rating Scale were increased from baseline. In 5 other patients with schizophrenia treated with oral haloperidol and rifampin, discontinuation of rifampin produced a mean 3.3-fold increase in haloperidol concentrations.

Carbamazepine

In a study in 11 patients with schizophrenia coadministered haloperidol and increasing doses of carbamazepine, haloperidol plasma concentrations decreased linearly with increasing carbamazepine concentrations.

During combination treatment with inducers of CYP3A4, it is recommended that patients be monitored and the haloperidol decanoate dose increased or the dosage interval adjusted, as deemed necessary. After withdrawal of the CYP3A4 inducer, the concentration of haloperidol may gradually increase and therefore it may be necessary to reduce the dose of haloperidol decanoate, or adjust the dosage interval.

Effect of Haloperidol on Other Drugs

Haloperidol is an inhibitor of CYP2D6. Plasma concentrations of CYP2D6 substrates (e,g. tricyclic antidepressants such as desipramine or imipramine) may increase when they are co-administered with haloperidol.

Carcinogenesis, Mutagenesis, and Impairment of Fertility

No mutagenic potential of haloperidol decanoate was found in the Ames Salmonella assay. Negative or inconsistent positive findings have been obtained in in vitroand in vivostudies of effects of short-acting haloperidol on chromosome structure and number. The available cytogenetic evidence is considered too inconsistent to be conclusive at this time.

Carcinogenicity studies using oral haloperidol were conducted in Wistar rats (dosed at up to 5 mg/kg daily for 24 months) and in Albino Swiss mice (dosed at up to 5 mg/kg daily for 18 months). In the rat study survival was reduced in all dose groups, decreasing the number of rats at risk for developing tumors. However, a relatively greater number of rats survived to the end of the study in high-dose male and female groups, these animals did not have a greater incidence of tumors than control animals. Therefore, although not optimal, this study does suggest the absence of a haloperidol related increase in the incidence of neoplasia in rats at doses up to approximately 2.5 times the maximum recommended human dose (MRHD) of 20 mg/day based on mg/m^2body surface area.

In female mice there was a statistically significant increase in mammary gland neoplasia and total tumor incidence at doses approximately 0.3 and 1.2 times the MRHD based on mg/m^2body surface area and there was a statistically significant increase in pituitary gland neoplasia at approximately 1.2 times the MRHD In male mice, no statistically significant differences in incidences of total tumors or specific tumor types were noted.

Antipsychotic drugs elevate prolactin levels; the elevation persists during chronic administration. Tissue culture experiments indicate that approximately one-third of human breast cancers are prolactin dependent in vitro, a factor of potential importance if the prescription of these drugs is contemplated in a patient with a previously detected breast cancer. Although disturbances such as galactorrhea, amenorrhea, gynecomastia, and impotence have been reported, the clinical significance of elevated serum prolactin levels is unknown for most patients.

An increase in mammary neoplasms has been found in rodents after chronic administration of antipsychotic drugs. Published epidemiologic studies have shown inconsistent results when exploring the potential association between hyperprolactinemia and breast cancer.

Usage in Pregnancy

Rats or rabbits administered oral haloperidol at doses of 0.5 to 7.5 mg/kg, which are approximately 0.2 to 7 times the maximum recommended human dose (MRHD) of 20 mg/day based on mg/m^2body surface area. showed an increase in incidence of resorption, reduced fertility, delayed delivery and pup mortality. No fetal abnormalities were observed at these doses in rats or rabbits.

Cleft palate has been observed in mice administered oral haloperidol at a dose of 0.5 mg/kg, which is approximately 0.1 times the MRHD based on mg/m^2body surface area.

There are no adequate and well-controlled studies in pregnant women. There are reports, however, of cases of limb malformations observed following maternal use of haloperidol along with other drugs which have suspected teratogenic potential during the first trimester of pregnancy. Causal relationships were not established with these cases. Since such experience does not exclude the possibility of fetal damage due to haloperidol, haloperidol decanoate should be used during pregnancy or in women likely to become pregnant only if the benefit clearly justifies a potential risk to the fetus.

Non-Teratogenic Effects

Neonates exposed to antipsychotic drugs (including haloperidol) during the third trimester of pregnancy are at risk for extrapyramidal and/or withdrawal symptoms following delivery. There have been reports of agitation, hypertonia, hypotonia, tremor, somnolence, respiratory distress, and feeding disorder in these neonates. These complications have varied in severity; while in some cases symptoms have been self-limited, in other cases neonates have required intensive care unit support and prolonged hospitalization.

Haloperidol decanoate should be used during pregnancy only if the potential benefit justifies the potential risk to the fetus.

Nursing Mothers

Since haloperidol is excreted in human breast milk, infants should not be nursed during drug treatment with haloperidol decanoate.

Pediatric Use

Safety and effectiveness of haloperidol decanoate in children have not been established.

Geriatric Use

Clinical studies of haloperidol did not include sufficient numbers of subjects aged 65 and over to determine whether they respond differently from younger subjects. Other reported clinical experience has not consistently identified differences in responses between the elderly and younger patients. However, the prevalence of tardive dyskinesia appears to be highest among the elderly, especially elderly women (see WARNINGS, Tardive Dyskinesia). Also, the pharmacokinetics of haloperidol in geriatric patients generally warrants the use of lower doses (see DOSAGE AND ADMINISTRATION).

Use in Hepatic Impairment

Studies in patients with hepatic impairment have not been conducted. Haloperidol concentrations may increase in hepatically impaired patients, because it is primarily metabolized by the liver and protein binding may decrease.

ADVERSE REACTIONS

The following adverse reactions are discussed in more detail in other sections of the labeling:

- WARNINGS, Increased mortality in Elderly Patients with Dementia-Related Psychosis
- WARNINGS, Cardiovascular Effects
- WARNINGS, Tardive Dyskinesia
- WARNINGS, Neuroleptic Malignant Syndrome
- WARNINGS, Hypersensitivity Reactions
- WARNINGS, Falls
- WARNINGS, Combined Use of Haloperidol and Lithium
- WARNINGS, General
- PRECAUTIONS, Leukopenia, Neutropenia, and Agranulocytosis
- PRECAUTIONS, Other
- PRECAUTIONS, Usage in Pregnancy

Clinical Trials Experience

Because clinical trials are conducted under widely varying conditions, adverse reaction rates observed in the clinical trials of a drug cannot be directly compared to rates in the clinical trials of another drug, and may not reflect the rates observed in practice.

The data described below reflect exposure to haloperidol in 410 patients who participated in 13 clinical trials with haloperidol decanoate (15 to 500 mg/month) in the treatment of schizophrenia or schizoaffective disorder. These clinical trials comprised:

- 1 double-blind, active comparator-controlled trial with fluphenazine decanoate.
- 2 trials comparing the decanoate formulation to oral haloperidol.
- 9 open-label trials.
- 1 dose-response trial.

The most common adverse reactions in haloperidol decanoate-treated patients in the double-blind, active comparator-controlled clinical trial with fluphenazine decanoate (≥5%) were: Parkinsonism, and oculogyric crisis.

Adverse Reactions Reported at ≥1% Incidence in a Double-Blind Active Comparator-Controlled Clinical Trial

Adverse reactions occurring in ≥1% of haloperidol decanoate-treated patients in a double-blind, clinical trial with the active comparator fluphenazine decanoate are shown in Table 1.

Table 1. Adverse Reactions Reported by ≥1% of Haloperidol Decanoate-treated Patients in a Double-Blind Active Comparator-Controlled Clinical Trial with Fluphenazine Decanoate
System/Organ Class Adverse Reaction | Haloperidol decanoate (n=36) % | Fluphenazine decanoate (n=36) %
Gastrointestinal Disorders
Abdominal pain | 2.8 | 0
Nervous System Disorders
Extrapyramidal disorder [Precise incidence for extrapyramidal disorder cannot be determined; reporting rates of some individual symptoms of extrapyramidal disorder are lower for haloperidol decanoate than for the active comparator, but the terms are included here because the events are considered associated with the drug] :
Parkinsonism | 30.6 | 44.4
Oculogyric crisis | 5.6 | 0
Akinesia | 2.8 | 22.2
Akathisia | 2.8 | 13.9
Tremor | 2.8 | 0
Headache | 2.8 | 0

Additional Adverse Reactions Reported in Double-Blind, Comparator, Open-Label and Dose-Response Clinical Trials

Additional adverse reactions that are listed below were reported by haloperidol decanoate-treated patients in comparator, open-label, and dose-response clinical trials, or at <1% incidence in a double-blind, active comparator-controlled clinical trial with fluphenazine decanoate.

Cardiac Disorders:Tachycardia

Endocrine Disorders:Hyperprolactinemia

Eye Disorders:Vision blurred

Gastrointestinal Disorders:Constipation, Dry mouth, Salivary hypersecretion

General Disorders and Administration Site Conditions:Injection site reaction

Investigations:Weight increased

Musculoskeletal and Connective Tissue Disorders:Muscle rigidity

Nervous System Disorders:Dyskinesia, Dystonia, Cogwheel rigidity, Hypertonia, Masked Facies, Sedation, Somnolence

Reproductive System and Breast Disorders:Erectile dysfunction

Adverse Reactions Identified in Clinical Trials with Haloperidol (Non-Decanoate Formulations)

The adverse reactions listed below were identified with non-decanoate formulations, and reflect exposure to the active moiety haloperidol in the following:

- 284 patients who participated in 3 double-blind, placebo-controlled clinical trials with haloperidol (injection or oral formulation, 2 to 20 mg/day); two trials were in the treatment of schizophrenia and one in the treatment of bipolar disorder.
- 1295 patients who participated in 16 double-blind, active comparator-controlled clinical trials with haloperidol (injection or oral formulation, 1 to 45 mg/day) in the treatment of schizophrenia.

Musculoskeletal and Connective Tissue Disorders:Torticollis, Trismus, Muscle twitching

Nervous System Disorders:Neuroleptic malignant syndrome, Tardive dyskinesia, Bradykinesia, Hyperkinesia, Hypokinesia, Dizziness, Nystagmus

Psychiatric Disorders:Loss of libido, Restlessness

Reproductive System and Breast Disorders:Amenorrhea, Galactorrhea, Dysmenorrhea, Menorrhagia, Breast discomfort

Skin and Subcutaneous Tissue Disorders:Acneiform skin reactions

Vascular Disorders:Hypotension, Orthostatic hypotension

Postmarketing Experience

The following adverse reactions relating to the active moiety haloperidol have been identified during postapproval use of haloperidol or haloperidol decanoate. Because these reactions are reported voluntarily from a population of uncertain size, it is not always possible to reliably estimate their frequency or establish a causal relationship to drug exposure.

Blood and Lymphatic System Disorders:Pancytopenia, Agranulocytosis, Thrombocytopenia, Leukopenia, Neutropenia

Cardiac Disorders:Ventricular fibrillation, Torsade de pointes, Ventricular tachycardia, Extrasystoles

Endocrine Disorders:Inappropriate antidiuretic hormone secretion

Gastrointestinal Disorders:Vomiting, Nausea

General Disorders and Administration Site Conditions:Sudden death, Face edema, Edema, Hyperthermia, Hypothermia, Injection site abscess

Hepatobiliary Disorders:Acute hepatic failure, Hepatitis, Cholestasis, Jaundice, Liver function test abnormal

Immune System Disorders:Anaphylactic reaction, Hypersensitivity

Investigations:Electrocardiogram QT prolonged, Weight decreased

Metabolic and Nutritional Disorders:Hypoglycemia

Musculoskeletal and Connective Tissue Disorders:Rhabdomyolysis

Nervous System Disorders:Convulsion, Opisthotonus, Tardive dystonia

Pregnancy, Puerperium and Perinatal Conditions:Drug withdrawal syndrome neonatal

Psychiatric Disorders:Agitation, Confusional state, Depression, Insomnia

Renal and Urinary Disorders:Urinary retention

Reproductive System and Breast Disorders:Priapism, Gynecomastia

Respiratory, Thoracic and Mediastinal Disorders:Laryngeal edema, Bronchospasm, Laryngospasm, Dyspnea

Skin and Subcutaneous Tissue Disorders:Angioedema, Dermatitis exfoliative, Hypersensitivity vasculitis, Photosensitivity reaction, Urticaria, Pruritus, Rash, Hyperhidrosis

OVERDOSAGE

While overdosage is less likely to occur with a parenteral than with an oral medication, information pertaining to haloperidol is presented, modified only to reflect the extended duration of action of haloperidol decanoate.

Manifestations

In general, the symptoms of overdosage would be an exaggeration of known pharmacologic effects and adverse reactions, the most prominent of which would be: 1) severe extrapyramidal reactions, 2) hypotension, or 3) sedation. The patient would appear comatose with respiratory depression and hypotension which could be severe enough to produce a shock-like state. The extrapyramidal reactions would be manifested by muscular weakness or rigidity and a generalized or localized tremor, as demonstrated by the akinetic or agitans types, respectively. With accidental overdosage, hypertension rather than hypotension occurred in a two-year old child. The risk of ECG changes associated with torsade de pointes should be considered.

(For further information regarding torsade de pointes, please refer to ADVERSE REACTIONS.)

Treatment

Since there is no specific antidote, treatment is primarily supportive. Dialysis is not recommended in the treatment of overdose because it removes only very small amounts of haloperidol. A patent airway must be established by use of an oropharyngeal airway or endotracheal tube or, in prolonged cases of coma, by tracheostomy. Respiratory depression may be counteracted by artificial respiration and mechanical respirators. Hypotension and circulatory collapse may be counteracted by use of intravenous fluids, plasma, or concentrated albumin, and vasopressor agents such as metaraminol, phenylephrine and norepinephrine. Epinephrine must not be used. In case of severe extrapyramidal reactions, antiparkinson medication should be administered, and should be continued for several weeks, and then withdrawn gradually as extrapyramidal symptoms may emerge. ECG and vital signs should be monitored especially for signs of Q-Tc interval prolongation or dysrhythmias and monitoring should continue until the ECG is normal. Severe arrhythmias should be treated with appropriate anti-arrhythmic measures.

In case of an overdose, consult a Certified Poison Control Center (1-800-222-1222).

DOSAGE AND ADMINISTRATION

Haloperidol decanoate 50 and Haloperidol decanoate 100 should be administered by deep intramuscular injection. A 21 gauge needle is recommended. The maximum volume per injection site should not exceed 3 mL. DO NOT ADMINISTER INTRAVENOUSLY.

Parenteral drug products should be inspected visually for particulate matter and discoloration prior to administration, whenever solution and container permit.

Haloperidol decanoate 50 and Haloperidol decanoate 100 are intended for use in schizophrenic patients who require prolonged parenteral antipsychotic therapy. These patients must be previously stabilized on antipsychotic medication before considering a conversion to haloperidol decanoate. Furthermore, it is recommended that patients being considered for haloperidol decanoate therapy have been treated with, and tolerate well, short-acting haloperidol in order to reduce the possibility of an unexpected adverse sensitivity to haloperidol. Close clinical supervision is required during the initial period of dose adjustment in order to minimize the risk of overdosage or reappearance of psychotic symptoms before the next injection. During dose adjustment or episodes of exacerbation of symptoms of schizophrenia, haloperidol decanoate therapy can be supplemented with short-acting forms of haloperidol.

The dose of Haloperidol decanoate 50 or Haloperidol decanoate 100 should be expressed in terms of its haloperidol content. The starting dose of haloperidol decanoate should be based on the patient's age, clinical history, physical condition, and response to previous antipsychotic therapy. The preferred approach to determining the minimum effective dose is to begin with lower initial doses and to adjust the dose upward as needed. For patients previously maintained on low doses of antipsychotics (e.g. up to the equivalent of 10 mg/day oral haloperidol), it is recommended that the initial dose of haloperidol decanoate be 10–15 times the previous daily dose in oral haloperidol equivalents; limited clinical experience suggests that lower initial doses may be adequate.

Initial Therapy

Conversion from oral haloperidol to haloperidol decanoate can be achieved by using an initial dose of haloperidol decanoate that is 10 to 20 times the previous daily dose in oral haloperidol equivalents.

In patients who are elderly, debilitated, or stable on low doses of oral haloperidol (e.g. up to the equivalent of 10 mg/day oral haloperidol), a range of 10 to 15 times the previous daily dose in oral haloperidol equivalents is appropriate for initial conversion.

In patients previously maintained on higher doses of antipsychotics for whom a low dose approach risks recurrence of psychiatric decompensation and in patients whose long-term use of haloperidol has resulted in a tolerance to the drug, 20 times the previous daily dose in oral haloperidol equivalents should be considered for initial conversion, with downward titration on succeeding injections.

The initial dose of haloperidol decanoate should not exceed 100 mg regardless of previous antipsychotic dose requirements. If, therefore, conversion requires more than 100 mg of haloperidol decanoate as an initial dose, that dose should be administered in two injections, i.e. a maximum of 100 mg initially followed by the balance in 3 to 7 days.

Maintenance Therapy

The maintenance dosage of haloperidol decanoate must be individualized with titration upward or downward based on therapeutic response. The usual maintenance range is 10 to 15 times the previous daily dose in oral haloperidol equivalents dependent on the clinical response of the patient.

HALOPERIDOL DECANOATE DOSING RECOMMENDATIONS
Monthly
Patients | 1stMonth | Maintenance
Stabilized on low daily oral doses (up to 10 mg/day) Elderly or Debilitated | 10–15 × Daily Oral Dose | 10–15 × Previous Daily Oral Dose
High dose Risk of relapse | 20 × Daily Oral Dose | 10–15 × Previous Daily Oral Dose
Tolerant to oral haloperidol

Close clinical supervision is required during initiation and stabilization of haloperidol decanoate therapy. Haloperidol decanoate is usually administered monthly or every 4 weeks. However, variation in patient response may dictate a need for adjustment of the dosing interval as well as the dose (see CLINICAL PHARMACOLOGY).

Clinical experience with haloperidol decanoate at doses greater than 450 mg per month has been limited.

INSTRUCTIONS FOR OPENING AMPULE

Step 1

- Medication often rests in the top part of the ampule. Before breaking the ampule, lightly tap the top of the ampule with your finger until all fluid moves to the bottom portion of the ampule. The ampule has a colored ring(s) and colored point which aids in the placement of fingers while breaking the ampule.

Step 2

- Hold the ampule between thumb and index finger with the colored point facing you.

Step 3

- Position the index finger of the other hand to support the neck of the ampule. Position the thumb so that it covers the colored point and is parallel to the colored ring(s).

Step 4

- Keeping the thumb on the colored point and with the index fingers close together, apply firm pressure on the colored point in the direction of the arrow to snap the ampule open.

HOW SUPPLIED

Haloperidol decanoate 50 for IM injection, 50 mg haloperidol as 70.52 mg per mL haloperidol decanoate:

NDC 10147-0921-3 - 3 × 1 mL ampules.

Haloperidol decanoate 100 for IM injection, 100 mg haloperidol as 141.04 mg per mL haloperidol decanoate:

NDC 10147-0922-5 - 5 × 1 mL ampules.

STORAGE AND HANDLING

Store at controlled room temperature (15°–30° C, 59°–86° F). Do not refrigerate or freeze.

Protect from light.

Keep out of reach of children.

Product of Belgium

Manufactured by:
Janssen Pharmaceutica NV
Beerse, Belgium

Or

GlaxoSmithKline Manufacturing S.p.A.
Parma, Italy

Manufactured for:
Patriot Pharmaceuticals, LLC
Horsham, PA 19044, USA

For patent information: www.janssenpatents.com

For more information, call 1-800-667-8570

Revised February 2025

© 2011 Patriot

PRINCIPAL DISPLAY PANEL - 50 mg/mL Box

NDC 10147-0921-3

IM Use
Only

HALOPERIDOL
Decanoate 50

50

INJECTION
50 mg/mL*

3 x 1-mL AMPULES Sterile

*Each mL contains 50 mg haloperidol
as 70.5 mg haloperidol decanoate in
a sesame oil vehicle, with 1.2% (w/v)
benzyl alcohol as a preservative.

Store at controlled room
temperature (15°–30°C, 59°–86°F).
Do not refrigerate or freeze.

Rx only.

For Intramuscular Use Only.

PROTECT FROM LIGHT.

For dosage and other prescribing
information, see accompanying
product literature.

The dose of Haloperidol Decanoate 50
should be expressed in terms of its
haloperidol content.

Dispense in a light-resistant container
as defined in the official compendium.

Keep out of reach of children

PATRIOT
PHARMACEUTICALSLLC

PRINCIPAL DISPLAY PANEL - 100 mg/mL Box

NDC 10147-0922-5

IM Use
Only

HALOPERIDOL
Decanoate 100

100

INJECTION
100 mg/mL*

5 x 1-mL AMPULES Sterile

*Each mL contains 100 mg haloperidol
as 141 mg haloperidol decanoate in a
sesame oil vehicle, with 1.2% (w/v)
benzyl alcohol as a preservative.

Store at controlled room
temperature (15°–30°C, 59°–86°F).
Do not refrigerate or freeze.

Rx only.

For Intramuscular Use Only.

PROTECT FROM LIGHT.

For dosage and other prescribing
information, see accompanying
product literature.

The dose of Haloperidol Decanoate 100
should be expressed in terms of its
haloperidol content.

Dispense in a light-resistant container
as defined in the official compendium.

Keep out of reach of children

PATRIOT
PHARMACEUTICALSLLC